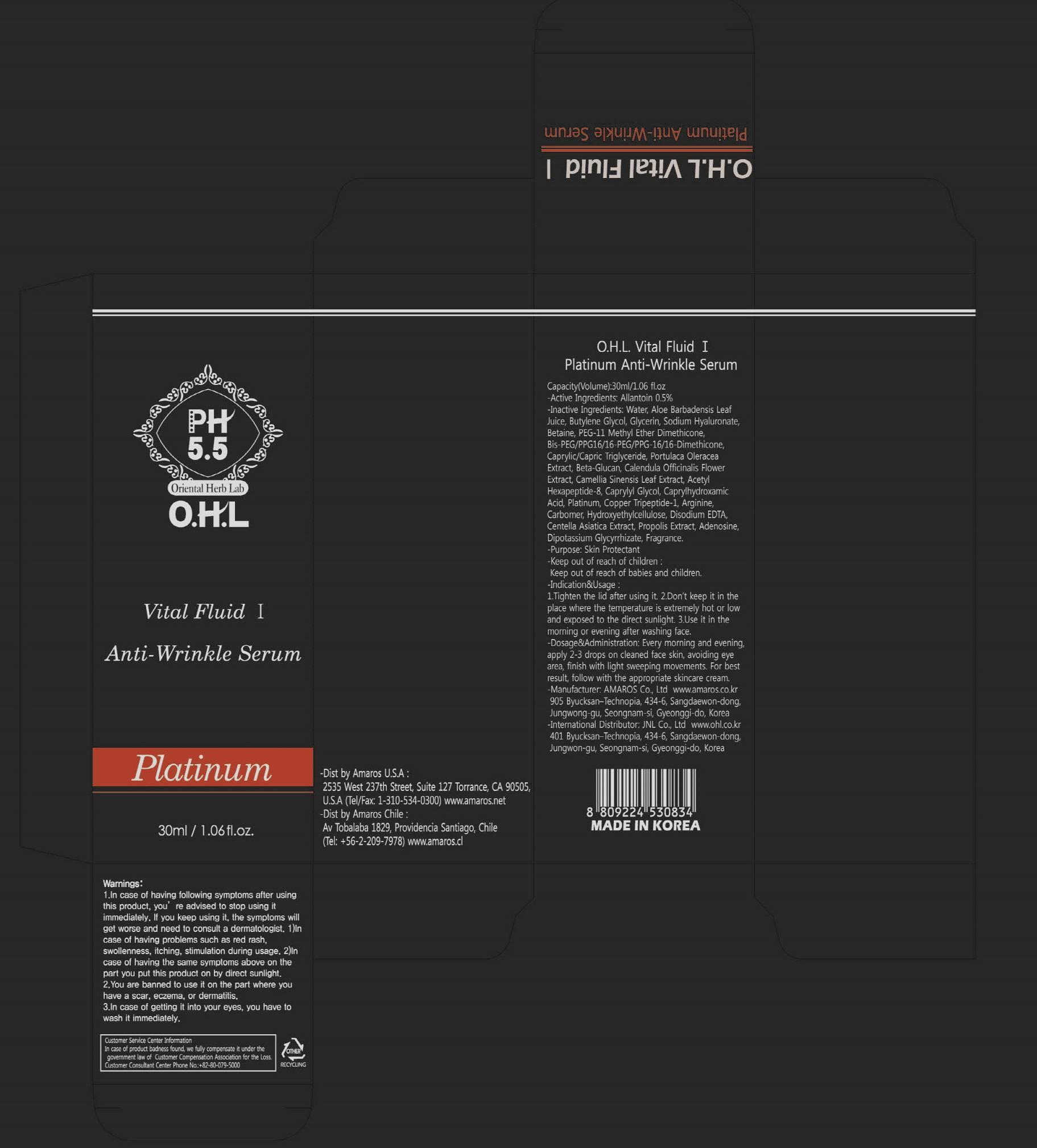 DRUG LABEL: Vital Fluid I Platinum Anti Wrinkle Serum
NDC: 60899-110 | Form: CREAM
Manufacturer: AMAROS CO., LTD.
Category: otc | Type: HUMAN OTC DRUG LABEL
Date: 20190411

ACTIVE INGREDIENTS: Allantoin 0.15 mg/30 mL
INACTIVE INGREDIENTS: Water; Glycerin

ACTIVE INGREDIENT

Active Ingredient: Allantoin 0.5%

INACTIVE INGREDIENT

Inactive Ingredients: Water, Aloe Barbadensis Leaf Juice, Butylene Glycol, Glycerin, Sodium Hyaluronate, Betaine, PEG-11 Methyl Ether Dimethicone, Bis-PEG/PPG16/16-PEG/PPG-16/16-Dimethicone, Caprylic/Capric Triglyceride, Portulaca Oleracea Extract, Beta-Glucan, Calendula Officinalis Flower Extract, Camellia Sinensis Leaf Extract, Acetyl Hexapeptide-8, Caprylyl Glycol, Caprylhydroxamic Acid, Platinum, Copper Tripeptide-1, Arginine, Carbomer, Hydroxyethylcellulose, Disodium EDTA, Centella Asiatica Extract, Propolis Extract, Adenosine, Dipotassium Glycyrrhizate, Fragrance.

PURPOSE

Purpose: Skin Protectant

WARNINGS

Warnings: 1. In case of having following symptoms after using this product, you're advised to stop using it immediately. If you keep using it, the symptoms will get worse and need to consult a dermatologist . 1) In case of having problems such as red rash, swollenness, itching, stimulation during usage. 2) In case of having the same symptoms above on the part you put this product on by direct sunlight. 2. You are banned to use it on the part where you have a scar, eczema, or dermatitis. 3. In case of getting it into your eyes, you have to wash it immediately.

Keep out of reach of children: Keep out of reach of babies and children.

INDICATIONS AND USAGE

Indication and Usage: 1. Tighten the lid after using it. 2. Don't keep it in the place where the temperature is extremely hot or low and exposed to the direct sunlight.3. Use it in the morning or evening after washing face.

Dosage and Administration: Every morning and evening, apply 2-3 drops on cleaned face skin, avoiding eye area, finish with light sweeping movements. For best result, follow with the appropriate skincare cream.